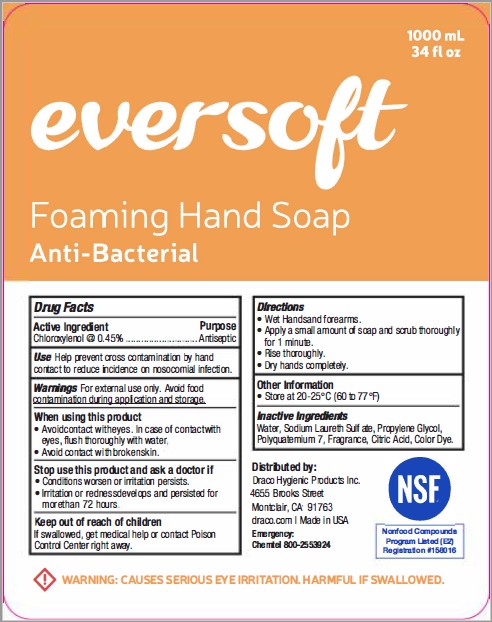 DRUG LABEL: EVERSOFT FOAMING HAND
NDC: 83019-101 | Form: SOAP
Manufacturer: Draco Hygienic Products Inc.
Category: otc | Type: HUMAN OTC DRUG LABEL
Date: 20241008

ACTIVE INGREDIENTS: CHLOROXYLENOL 0.45 g/100 mL
INACTIVE INGREDIENTS: WATER; SODIUM LAURETH SULFATE; PROPYLENE GLYCOL; ANHYDROUS CITRIC ACID; POLYQUATERNIUM-7 (70/30 ACRYLAMIDE/DADMAC; 1600 KD)

DRACO (as PLD) - EVERSOFT FOAMING HAND SOAP (83019-101)

ACTIVE INGREDIENT

Chloroxylenol @ 0.45%

PURPOSE

ANTISEPTIC

USE

Help prevent cross contaminatioo by hand contact to reduce inlcidence on nosocomial infection.

WARNINGS

For external use only. Avoid food contamination during application and storage.

When using this product

- Avoidcontact witheyes. ln case of contact wlth eyes, flush thoroughly with water
- Avoid contact with broken skin.

Stop use this product and ask a doctor if

- Conditions worsen or irritation persists.
- lrritation or redness develops and persisted for more than 72 hours

Keep out of reach of children
lf swallowed,get medical help or contact Poison Control Center right away.

DIRECTIONS

- Wet Hands and forearms.
- Apply a small amount of soap and scrub thoroughly for 1 minute.
- Rinse thoroughly.
- Dry hands completely.

OTHER INFORMATION

- Store at 20-25°C (60 to 77°F)

INACTIVE INGREDIENTS

Water, Sodium Laureth Sulfate, Propylene Glycol, Polyquatemium 7, Fragrance, Citric Acid, Color Dye.